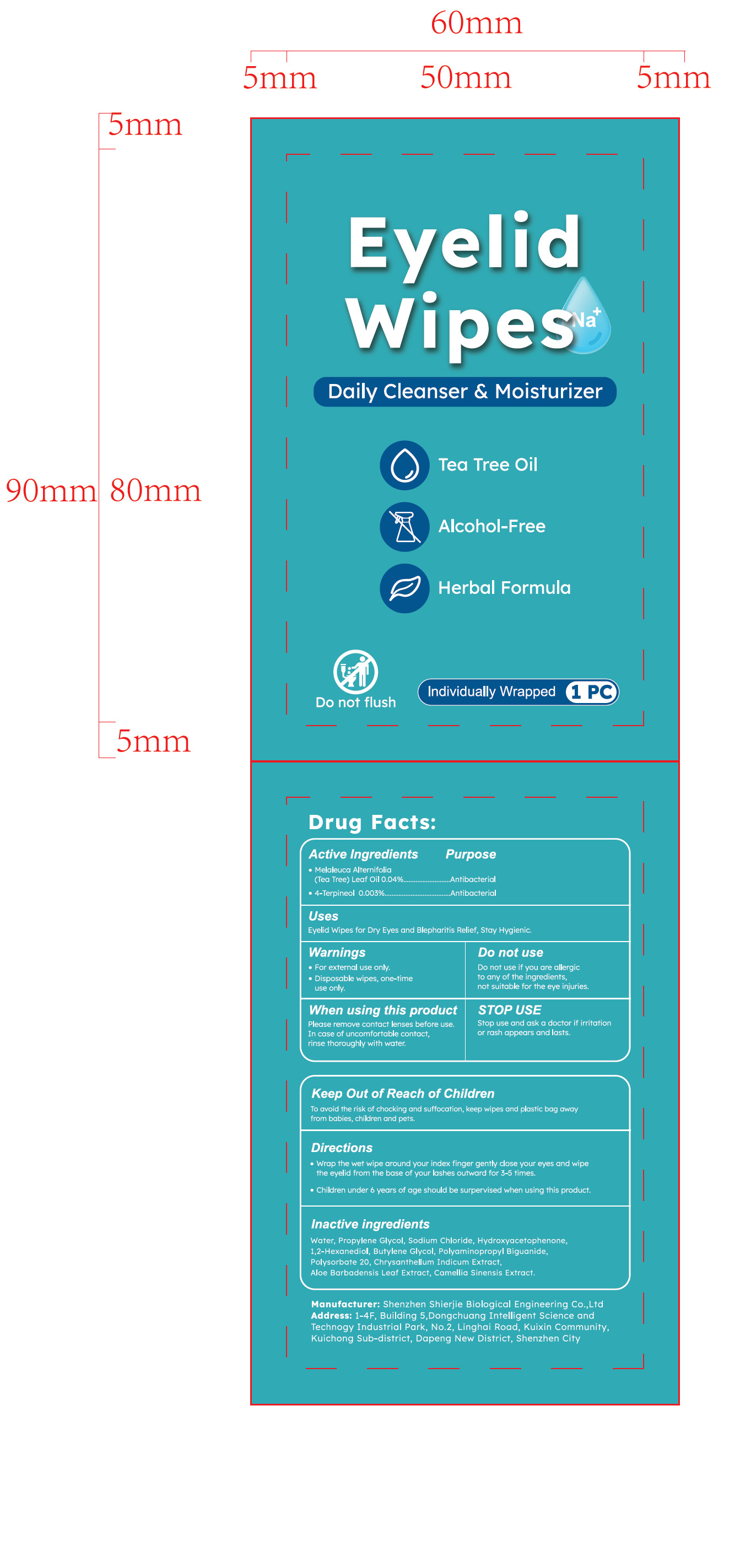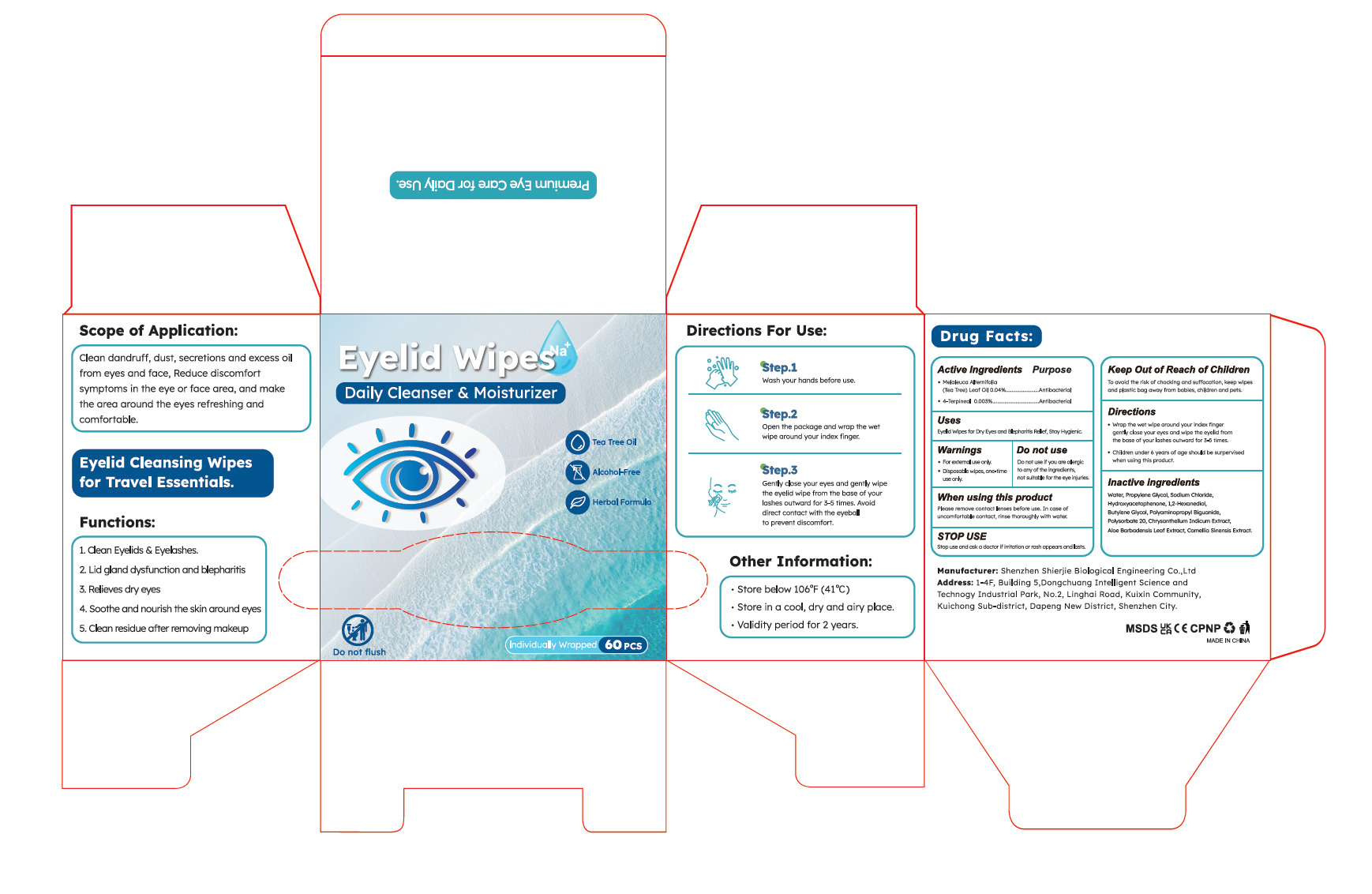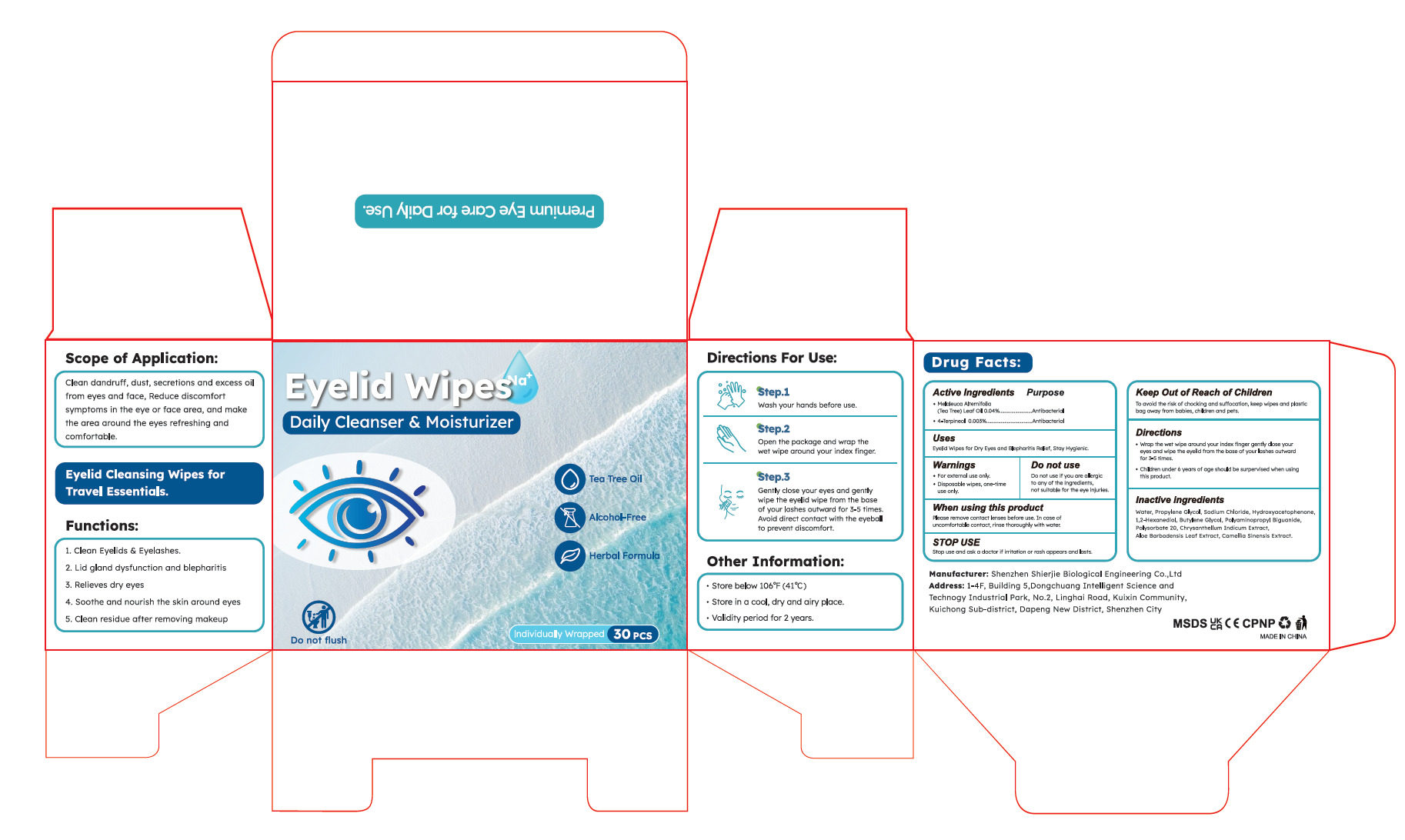 DRUG LABEL: Eyelid Wipes
NDC: 43116-040 | Form: CLOTH
Manufacturer: Shenzhen Shierjie Biological Engineering Co., LTD
Category: otc | Type: HUMAN OTC DRUG LABEL
Date: 20250608

ACTIVE INGREDIENTS: 4-TERPINEOL 0.003 U/100 U; MELALEUCA ALTERNIFOLIA (TEA TREE) LEAF OIL 0.04 U/100 U
INACTIVE INGREDIENTS: CAMELLIA SINENSIS LEAF; HYDROXYACETOPHENONE; CHRYSANTHELLUM INDICUM TOP; WATER; PROPYLENE GLYCOL; BUTYLENE GLYCOL; SODIUM CHLORIDE; POLYAMINOPROPYL BIGUANIDE; ALOE BARBADENSIS LEAF; POLYSORBATE 20; 1,2-HEXANEDIOL

43116-040

Active Ingredient

Melaleuca Alternifolia(Tea Tree)Leaf Oil 0.04%

4-Terpineol 0.003%

Purpose

Antibacterial

Use

Eyelid Wipes for Dry Eyes and Blepharitis Relief, Stay Hygienic.

Warnings

●For external use only.
●Disposable wipes, one-time use only.

Do not use if you are allergic to any of the ingredients, not suitable for the eye injuries.

When Using

Please remove contact lenses before use. In case of uncomfortable contact, rinse thoroughly with water.

Stop Use

Stop use and ask a doctor if irritation or rash appears and lasts.

Keep Oot Of Reach Of Children

To avoid the risk of chocking and suffocation, keep wipes and plastic bag away
from babies, children and pets.

Directions

●Wrap the wet wipe around your index finger gently close your eyes and wipe
the eyelid from the base of your lashes outward for 3-5 times.
●Children under 6 years of age should be surpervised when using this product.

Other information

●Store below 106°F (41°C)
●Store in a cool, dry and airy place.
●Validity period for 2 years.

Inactive ingredients

Water, Propylene Glycol, Sodium Chloride, Hydroxyacetophenone,
1,2-Hexanediol, Butylene Glycol, PolyaminopropyI Biguanide,
Polysorbate 20, Chrysanthellum Indicum Extract,
Aloe Barbadensis Leaf Extract, Camellia Sinensis Extract.